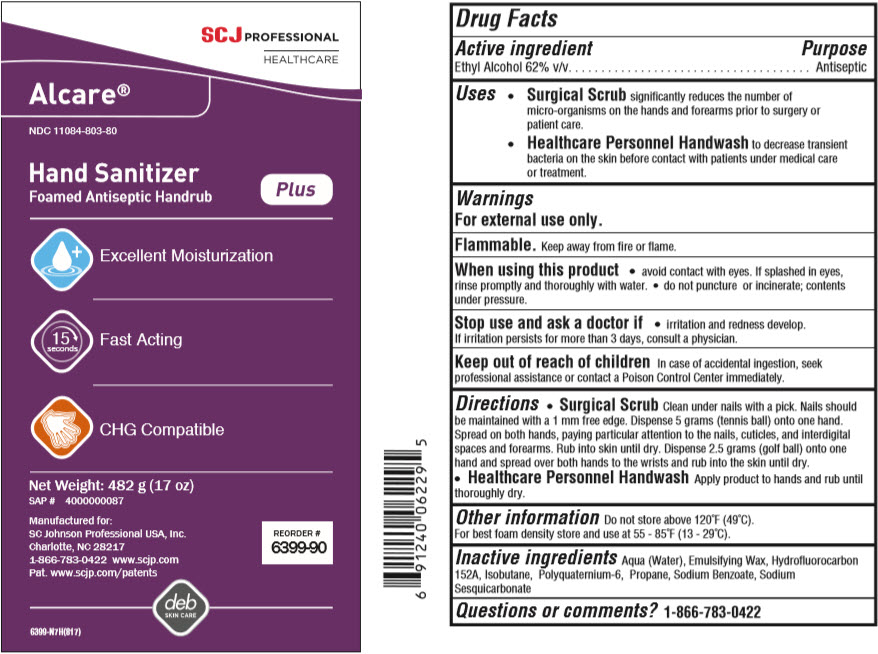 DRUG LABEL: Alcare Plus Foamed Antiseptic Handrub
NDC: 11084-803 | Form: AEROSOL, FOAM
Manufacturer: SC Johnson Professional USA, Inc.
Category: otc | Type: HUMAN OTC DRUG LABEL
Date: 20251222

ACTIVE INGREDIENTS: ALCOHOL 62 g/100 g
INACTIVE INGREDIENTS: WATER; 1,1-DIFLUOROETHANE; ISOBUTANE; CETOSTEARYL ALCOHOL; POLYSORBATE 60; POLYQUATERNIUM-6 (15000 MW); SODIUM BENZOATE; PROPANE; SODIUM SESQUICARBONATE

Alcare® Plus Foamed Antiseptic Handrub

Drug Facts

Active ingredient

Ethyl Alcohol 62% v/v

Purpose

Antiseptic

Uses

- Surgical Scrub significantly reduces the number of micro-organisms on the hands and forearms prior to surgery or patient care.
- Healthcare Personnel Handwash to decrease transient bacteria on the skin before contact with patients under medical care or treatment.

Warnings

For external use only.

Flammable. Keep away from fire or flame.

When using this product

- avoid contact with eyes. If splashed in eyes, rinse promptly and thoroughly with water.
- do not puncture or incinerate; contents under pressure.

Stop use and ask a doctor if

- irritation and redness develop. If irritation persists for more than 3 days, consult a physician.

Keep out of reach of children In case of accidental ingestion, seek professional assistance or contact a Poison Control Center immediately.

Directions

- Surgical Scrub Clean under nails with a pick. Nails should be maintained with a 1 mm free edge. Dispense 5 grams (tennis ball) onto one hand. Spread on both hands, paying particular attention to the nails, cuticles, and interdigital spaces and forearms. Rub into skin until dry. Dispense 2.5 grams (golf ball) onto one hand and spread over both hands to the wrists and rub into the skin until dry.
- Healthcare Personnel Handwash Apply product to hands and rub until thoroughly dry.

Other information

Do not store above 120°F (49°C). For best foam density store and use at 55 - 85°F (13 - 29°C).

Inactive ingredients

Aqua (Water), Emulsifying Wax, Hydroﬂuorocarbon 152A, Isobutane, Polyquaternium-6, Propane, Sodium Benzoate, Sodium Sesquicarbonate

Questions or comments?

1-866-783-0422

PRINCIPAL DISPLAY PANEL - 482 g Can Label

SCJ
PROFESSIONAL
HEALTHCARE

Alcare®

NDC 11084-803-80

Hand Sanitizer
Foamed Antiseptic Handrub

Plus

Excellent Moisturization

15 seconds
Fast Acting

CHG Compatible

Net Weight: 482 g (17 oz)

SAP # 4000000087

Manufactured for:
SC Johnson Professional USA, Inc.
Charlotte, NC 28217
1-866-783-0422 www.scjp.com
Pat. www.scjp.com/patents

deb
SKIN CARE

6399-N7H(817)

REORDER #
6399-90